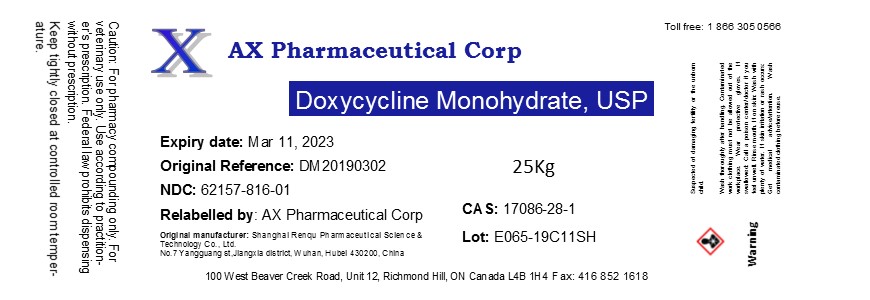 DRUG LABEL: Doxycycline Monohydrate
NDC: 62157-816 | Form: POWDER
Manufacturer: AX Pharmaceutical Corp
Category: other | Type: BULK INGREDIENT
Date: 20190411

ACTIVE INGREDIENTS: DOXYCYCLINE 1 kg/1 kg

Doxycycline Monohydrate